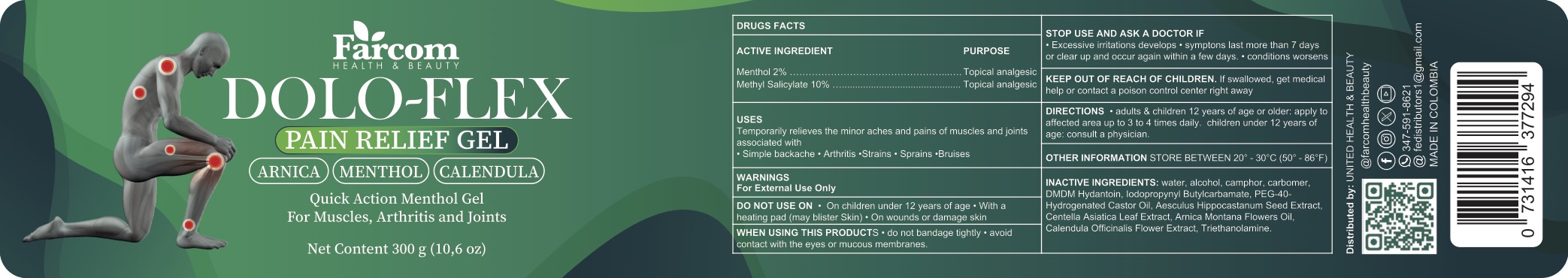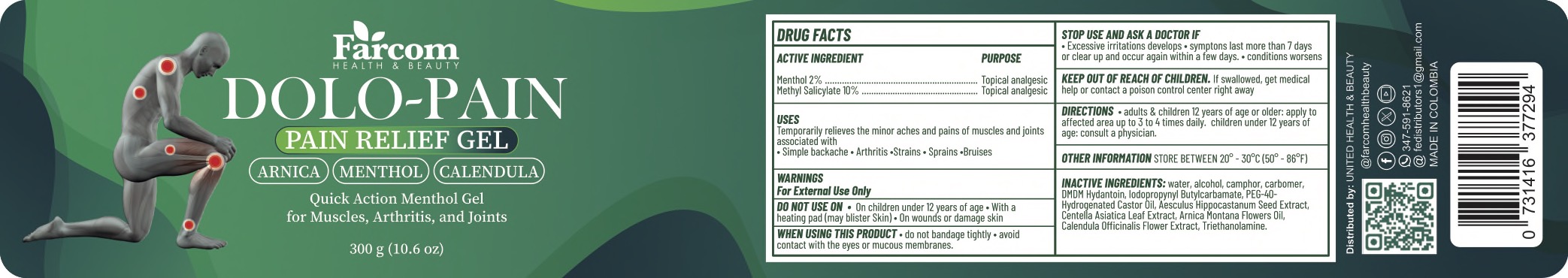 DRUG LABEL: Doloflex Pain Relief
NDC: 85350-039 | Form: GEL
Manufacturer: United Health & Beauty Corp
Category: otc | Type: HUMAN OTC DRUG LABEL
Date: 20251012

ACTIVE INGREDIENTS: MENTHOL 2 g/100 g; METHYL SALICYLATE 10 g/100 g
INACTIVE INGREDIENTS: ARNICA MONTANA FLOWER; PEG-40 HYDROGENATED CASTOR OIL; DMDM HYDANTOIN; HORSE CHESTNUT; CALENDULA OFFICINALIS FLOWER; CAMPHOR (SYNTHETIC); IODOPROPYNYL BUTYLCARBAMATE; TRIETHANOLAMINE; WATER; ALCOHOL; CENTELLA ASIATICA LEAF; CARBOMER 940

Doloflex Pain Relief

ACTIVE INGREDIENT

Menthol 2%, Methyl Salicylate 10%

PURPOSE

Topical Analgesic

INDICATIONS AND USAGE

Temporarily relieves the minor aches and pain of muscles and joints associated with simple backache, arthritis, strains, sprains, and bruises.

WARNINGS

For external use only.

Do not use on children under 12 years of age, with a heating pad (may blister skin), on wounds or damaged skin.

When using this product do not bandage tightly, avoid contact with the eyes or mucous membranes.

Stop use and ask a doctor if excessive irritation develops, symptoms last more than 7 days or clear up and occur again within a few days, condition worsens.

KEEP OUT OF REACH OF CHILDREN

If swallowed, get medical help or contact a poison control center right away.

DOSAGE AND ADMINISTRATION

Adults and children 12 years of age or older: apply to affected area up to 3 to 4 times daily. Children under 12 years of age: consult a physician.

INACTIVE INGREDIENT

Water, alcohol, carbomer, DMDM Hydantoin, Iodopropynyl Butylcarbamate, PEG-40 Hydrogenated Caster Oil, Aesculus Hippocastanum Seed Extract, Centella Assiatica Leaf Extract, Arnica Montana Flowers Oil, Calendula Officinalis Flower Extract, Triethanolamine.